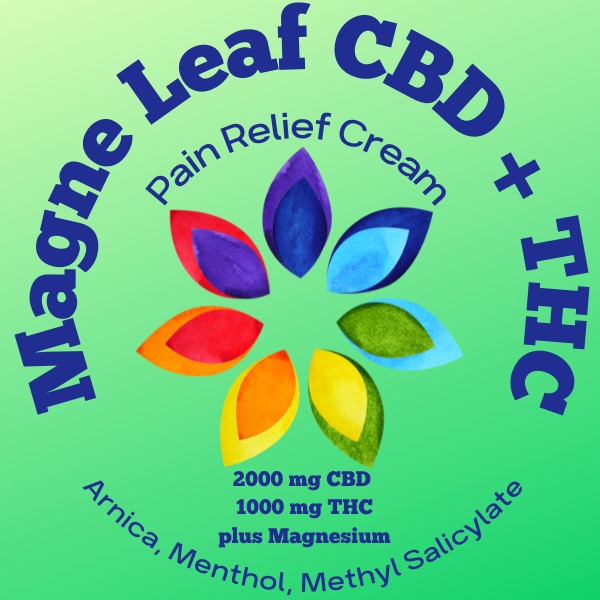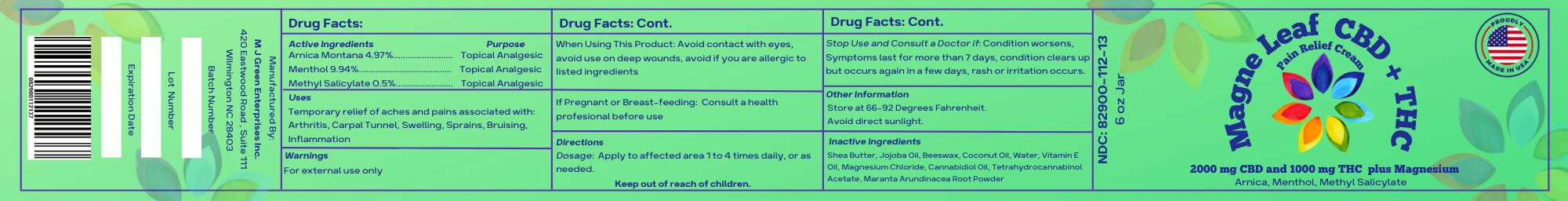 DRUG LABEL: MagneLeaf CBD THC
NDC: 82900-112 | Form: CREAM
Manufacturer: M J Green Enterprises, INC.
Category: homeopathic | Type: HUMAN OTC DRUG LABEL
Date: 20221122

ACTIVE INGREDIENTS: WATER 8.79 g/170.96 g; MENTHOL 17 g/170.96 g; CANNABIDIOL 2 g/170.96 g; MARANTA ARUNDINACEA ROOT 1 g/170.96 g; ARNICA MONTANA 8.5 g/170.96 g; ALPHA-TOCOPHEROL 6.52 g/170.96 g; METHYL SALICYLATE 1 g/170.96 g
INACTIVE INGREDIENTS: MAGNESIUM CHLORIDE 4.25 g/170.96 g; COCONUT OIL 12.4 g/170.96 g; PEG-8 BEESWAX 12.4 g/170.96 g; SHEA BUTTER 48.05 g/170.96 g; JOJOBA OIL 48.05 g/170.96 g; .DELTA.9-TETRAHYDROCANNABINOL ACETATE 1 g/170.96 g

MagneLeaf with CBD+THC

Active Ingredients

Menthol 9.94%

Arnica Montana 4.97%

Methyl Salicylate 0.5%

Purpose

Topical Analgesic

Uses

Temporary relief of aches and pains associated with, arthritis, carpal tunnel, swelling, sprains, bruising, inflammation

Warnings

For external use only

When Using This Product

Do not apply to wounds or irritated skin. Avoid contact with eyes, avoid use on deep wounds, avoid if you are allergic to listed ingredients.

Stop Use and consult a doctor if:

Condition worsens, Symptoms last for more than 7 days, condition clears up but occurs again in a few days, rash or irritation occurs.

If Pregnant of Breast-Feeding:

Consult a health professional before use

Directions

Dosage: Apply to affected area 1 to 4 times daily, or as needed.

Keep Out of Reach of Children

Other Information

Store at 66-92 Degrees Fahrenheit.

Avoid direct sunlight.

Inactive Ingredients

Shea Butter, Jojoba Oil, Beeswax, Coconut Oil, Water, Vitamin E Oil, Magnesium Chloride, Cannabidiol Oil, Tetrahydrocannabinol Acetate, Maranta Arundinacea Root Powder

6 ounce jar label

MagneLeaf Pain Relief CBD THC Label

6 ounce lid label

MagneLeaf THC Pain Relief Lid Label